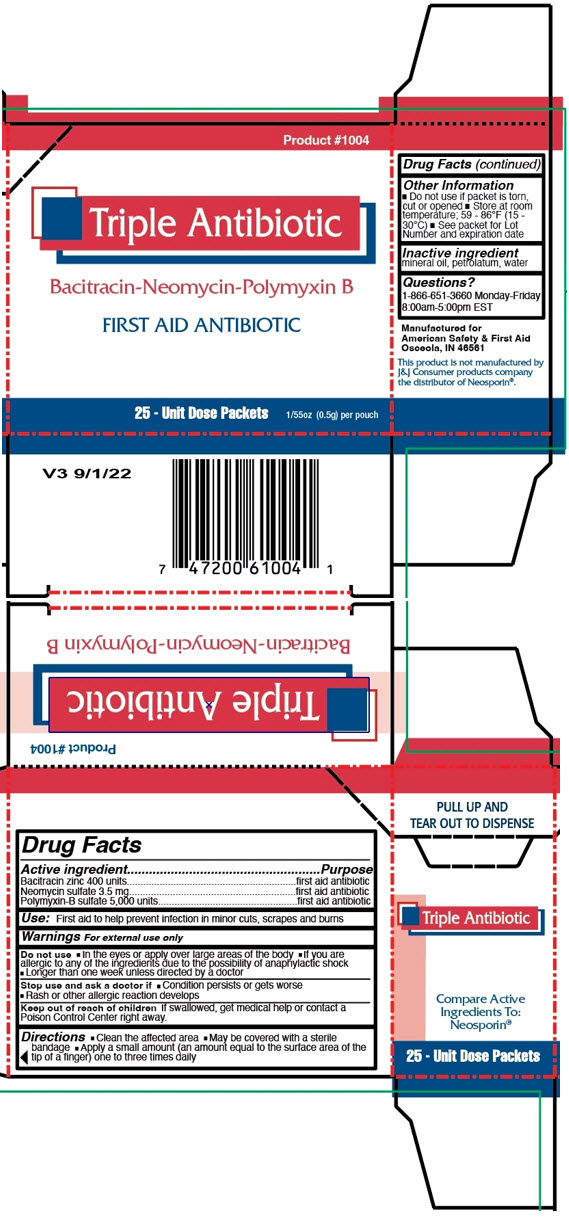 DRUG LABEL: TRIPLE ANTIBIOTIC
NDC: 73598-1004 | Form: OINTMENT
Manufacturer: JHK Inc dba American Safety & First Aid
Category: otc | Type: HUMAN OTC DRUG LABEL
Date: 20240426

ACTIVE INGREDIENTS: BACITRACIN ZINC 400 [iU]/0.5 g; NEOMYCIN SULFATE 3.5 mg/0.5 g; POLYMYXIN B SULFATE 5000 [iU]/0.5 g
INACTIVE INGREDIENTS: MINERAL OIL; PETROLATUM; WATER

TRIPLE ANTIBIOTIC

Drug Facts

ACTIVE INGREDIENT

Active ingredient | Purpose
Bacitracin zinc 400 units | first aid antibiotic
Neomycin sulfate 3.5 mg | first aid antibiotic
Polymyxin-B sulfate 5,000 units | first aid antibiotic

Use

First aid to help prevent infection in minor cuts, scrapes and burns

Warnings

For external use only

Do not use

- In the eyes or apply over large areas of the body
- If you are allergic to any of the ingredients due to the possibility of anaphylactic shock
- Longer than one week unless directed by a doctor

Stop use and ask a doctor if

- Condition persists or gets worse
- Rash or other allergic reaction develops

Keep out of reach of children

If swallowed, get medical help or contact a Poison Control Center right away.

Directions

- Clean the affected area
- May be covered with a sterile bandage
- Apply a small amount (an amount equal to the surface area of the tip of a finger) one to three times daily

Other Information

- Do not use if packet is torn, cut or opened
- Store at room temperature; 59 - 86°F (15 - 30°C)
- See packet for Lot Number and expiration date

Inactive ingredient

mineral oil, petrolatum, water

Questions?

1-866-651-3660 Monday-Friday 8:00am-5:00pm EST

PRINCIPAL DISPLAY PANEL - 25 Packet Box

Product #1004

Triple Antibiotic

Bacitracin-Neomycin-Polymyxin B

FIRST AID ANTIBIOTIC

25 - Unit Dose Packets

1/55oz (0.5g) per pouch